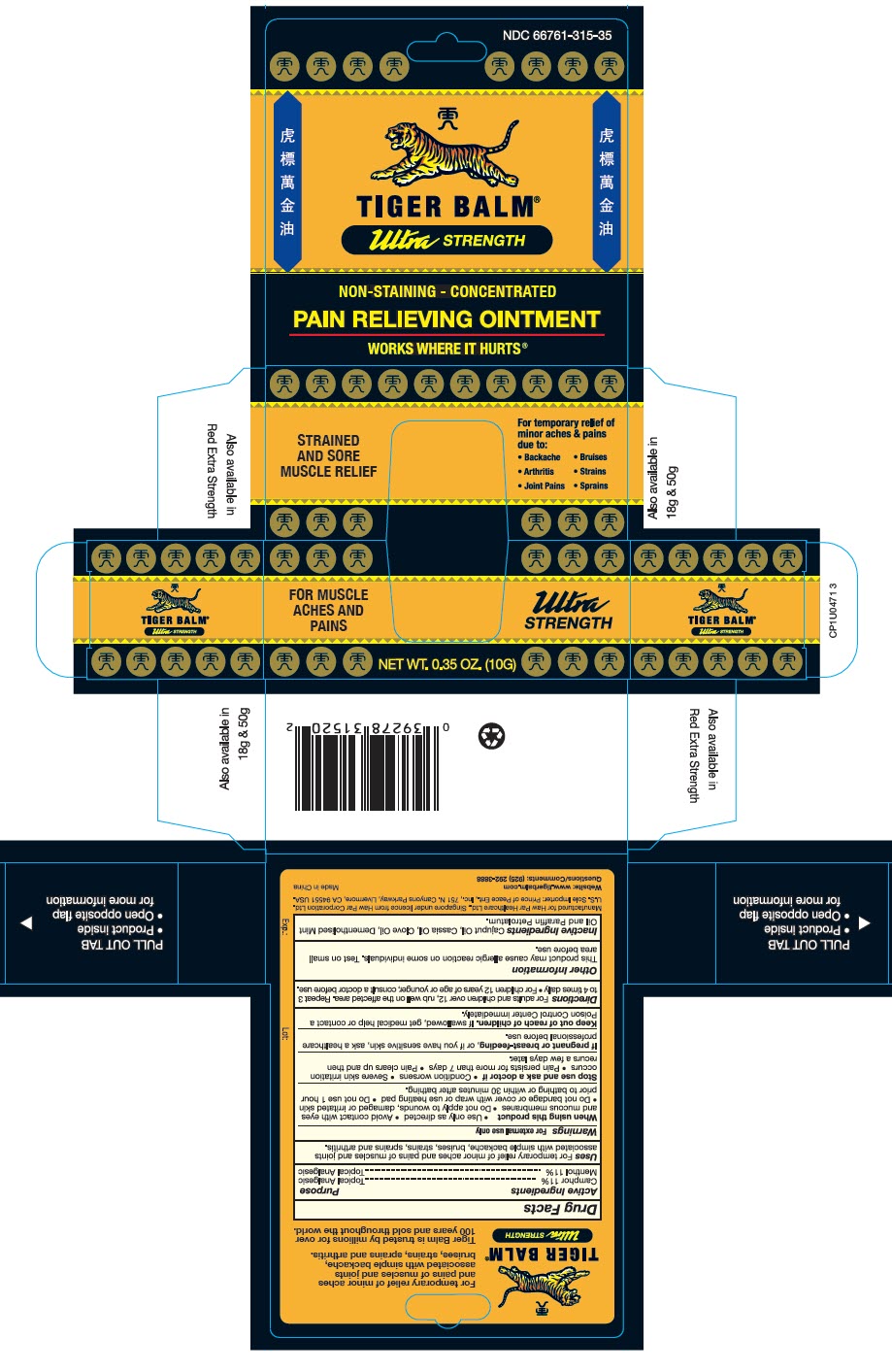 DRUG LABEL: Tiger Balm 
NDC: 66761-315 | Form: OINTMENT
Manufacturer: Haw Par Healthcare Ltd.
Category: otc | Type: HUMAN OTC DRUG LABEL
Date: 20251217

ACTIVE INGREDIENTS: Camphor (Synthetic) 110 mg/1 g; Menthol, Unspecified Form 110 mg/1 g
INACTIVE INGREDIENTS: Cajuput oil; Chinese Cinnamon Oil; Clove oil

TIGER BALM®
Ultra STRENGTH

Drug Facts

ACTIVE INGREDIENT

Active Ingredients | Purpose
Camphor 11% | Topical Analgesic
Menthol 11% | Topical Analgesic

Uses

For temporary relief of minor aches and pains of muscles and joints associated with simple backache, bruises, strains, sprains and arthritis.

Warnings

For External Use Only

When using this product

- Use only as directed
- Avoid contact with eyes and mucous membranes
- Do not apply to wounds, damaged or irritated skin
- Do not bandage or cover with wrap or use heating pad
- Do not use 1 hour prior to bathing or within 30 minutes after bathing.

Stop use and ask a doctor if

- Condition worsens
- Severe skin irritation occurs
- Pain persists for more than 7 days
- Pain clears up and then recurs a few days later.

PREGNANCY OR BREAST FEEDING

If pregnant or breast-feeding, or if you have sensitive skin, ask a healthcare professional before use.

Keep out of reach of children. If swallowed, get medical help or contact a Poison Control Center immediately.

Directions

- For adults and children over 12, rub well on the affected area. Repeat 3 to 4 times daily
- For children 12 years of age or younger, consult a doctor before use.

Other information

This product may cause allergic reaction on some individuals. Test on small area before use.

Inactive Ingredients

Cajuput Oil, Cassia Oil, Clove Oil, Dementholized Mint Oil and Paraffin Petrolatum.

Manufactured by Haw Par Healthcare Ltd., Singapore under license from Haw Par Corporation Ltd.

Questions

(510) 887-1899

PRINCIPAL DISPLAY PANEL - 10 G Jar Box

NDC 66761-315-35

TIGER BALM®
Ultra STRENGTH

NON-STAINING - CONCENTRATED
PAIN RELIEVING OINTMENT
WORKS WHERE IT HURTS®

FOR MUSCLE
ACHES AND
PAINS

Ultra
STRENGTH

NET WT. 0.35 OZ. (10G)